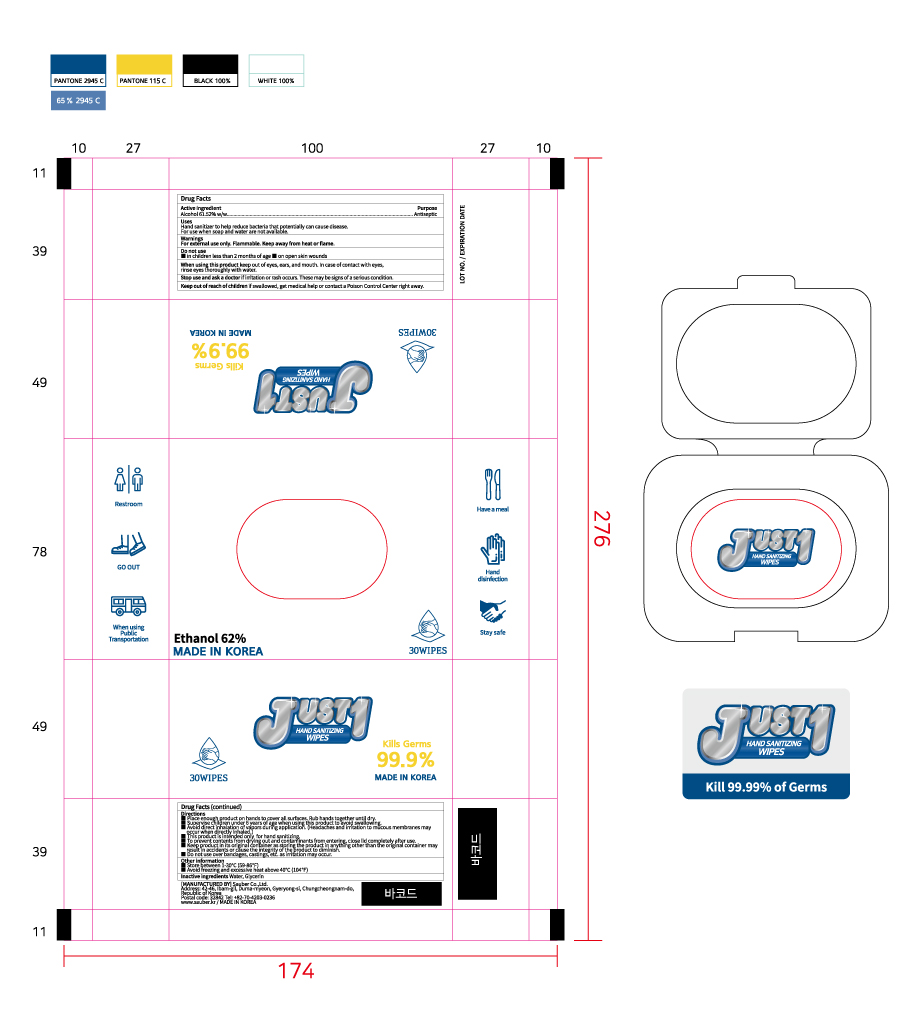 DRUG LABEL: Just 1
NDC: 78880-612 | Form: CLOTH
Manufacturer: Sauber Co.,Ltd.
Category: otc | Type: HUMAN OTC DRUG LABEL
Date: 20210108

ACTIVE INGREDIENTS: ALCOHOL 1.79 g/1 1
INACTIVE INGREDIENTS: WATER; GLYCERIN

[Active ingredient strength unit added] Just 1 | 30 WIPES IN 1 PACKET | 78880-612-30 | HAND SANITIZING WIPES